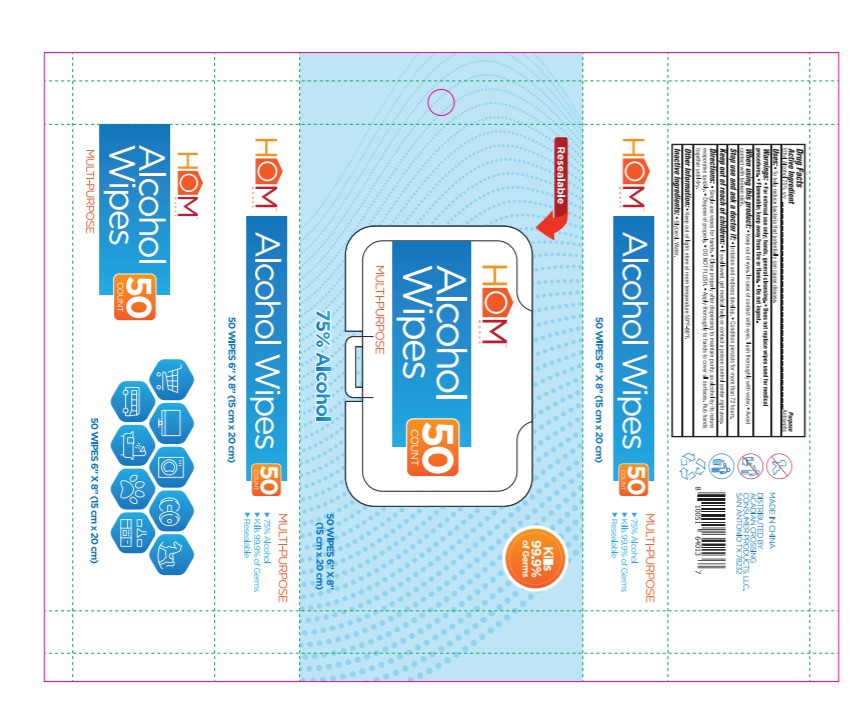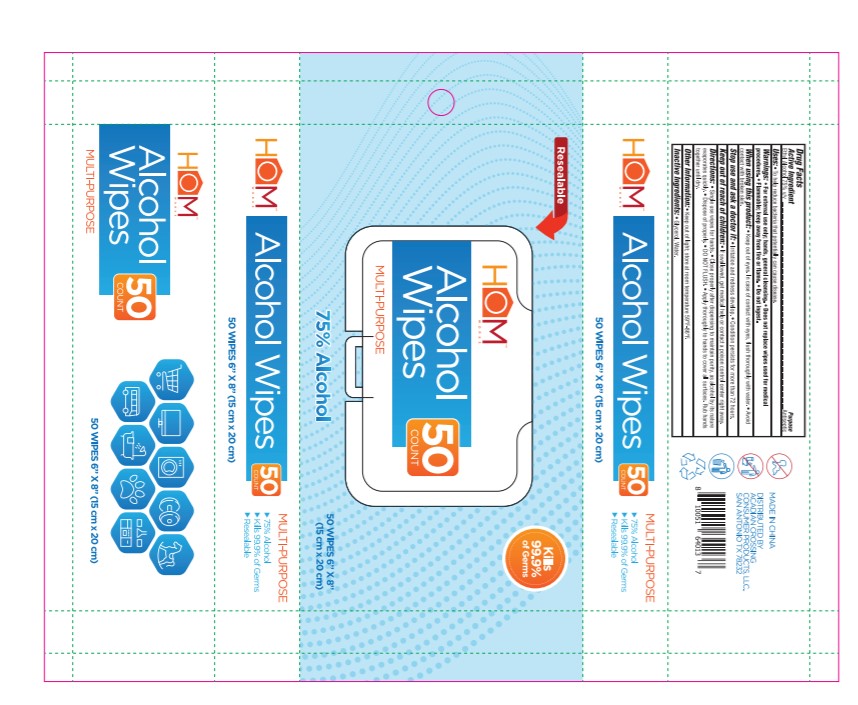 DRUG LABEL: Sanitizer Wipes
NDC: 76830-501 | Form: LIQUID
Manufacturer: Organic Filling Solutions, LLC
Category: otc | Type: HUMAN OTC DRUG LABEL
Date: 20200820

ACTIVE INGREDIENTS: ALCOHOL 172.5 mL/230 mL
INACTIVE INGREDIENTS: GLYCERIN 7.5 mL/230 mL; WATER

This is an alcohol wipe manufactured in the USA

1. Alcohol (ethanol) (USP or Food Chemical Codex (FCC) grade) (75%, volume/volume (v/v)) in an aqueous solution denatured according to Alcohol and Tobacco Tax and Trade Bureau regulations in 27 CFR part 20.
2. Glycerol (3.2% v/v)
3. Sterile distilled water or boiled cold water.

The firm does not add other active or inactive ingredients. Different or additional ingredients may impact the quality and potency of the product.

Active Ingredient(s)

Alcohol 75% v/v. Purpose: Antiseptic

Purpose

Multi-purpose

Use

Single use wipes for hands. Close properly after dispensing to maintain purity, as alcohol by nature evaporates quickly. Dispose properly. Apply thoroughly to hands to cover all surfaces. Rub hands together until dry.

Warnings

For external use only, hands, general cleaning. Does not replace wipes for medical procedures. Flammable; keep away from fire or flame. Do not ingest.

Do not use

- Stop use and ask a doctor if irritation and redness develop, condition persists for more than 72 hours
- Keep out of reach of children. If swallowed, get medical help or contact a poison control center right away.

When using this product, keep out of eyes. In case of contact with eyes, flush thoroughly with water. Avoid contact with broken skin.

Stop use and ask a doctor if irritation or redness develop. Condition persists for more than 72 hours

Keep out of reach of children. If swallowed, get medical help or contact a Poison Control Center right away.

Directions

- Apply thoroughly to hands to cover all surfaces. Rub hands together until dry.

Other information

- Keep out of light, store at room temperature 59 - 86 degrees Farenheit

Inactive ingredients

glycerin, purified water USP

RECENT MAJOR CHANGES

Single wipe use. Apply thoroughly to hands to cover all surfaces. Rub hands together until dry.

Package Label - Principal Display Panel

230 mL NDC: 76830-501-07